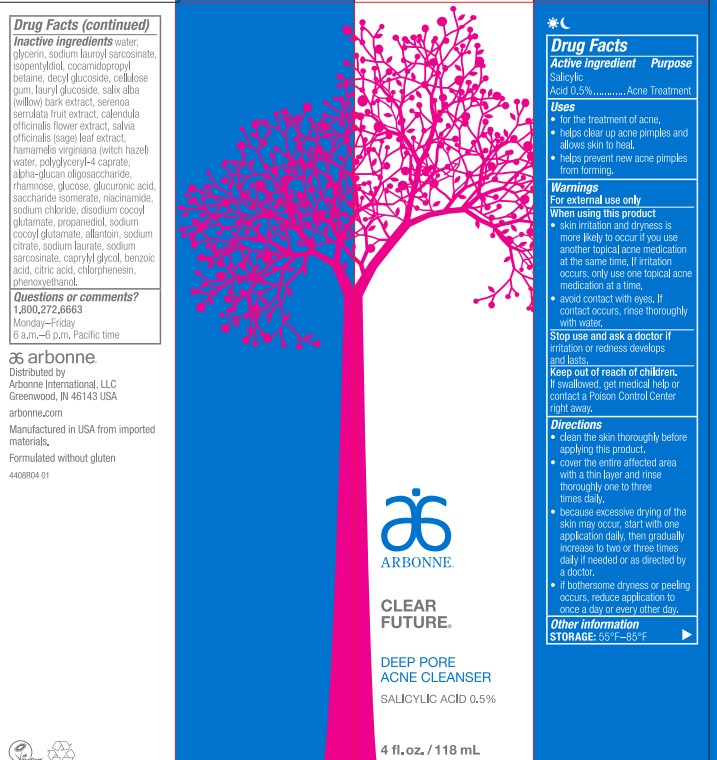 DRUG LABEL: Clear Future Deep Pore Cleanser
NDC: 42508-904 | Form: GEL
Manufacturer: Arbonne International, LLC
Category: otc | Type: HUMAN OTC DRUG LABEL
Date: 20251203

ACTIVE INGREDIENTS: SALICYLIC ACID 0.5 mg/118 mL
INACTIVE INGREDIENTS: GLYCERIN; SODIUM LAUROYL SARCOSINATE; ISOPENTYLDIOL; COCAMIDOPROPYL BETAINE; DECYL GLUCOSIDE; CARBOXYMETHYLCELLULOSE SODIUM, UNSPECIFIED; LAURYL GLUCOSIDE; SALIX ALBA BARK; WATER; SAW PALMETTO; CALENDULA OFFICINALIS FLOWER; SAGE; HAMAMELIS VIRGINIANA TOP WATER; POLYGLYCERYL-4 CAPRATE; .ALPHA.-GLUCAN OLIGOSACCHARIDE; RHAMNOSE; DEXTROSE, UNSPECIFIED FORM; GLUCURONIC ACID; SACCHARIDE ISOMERATE; NIACINAMIDE; SODIUM CHLORIDE; DISODIUM COCOYL GLUTAMATE; PROPANEDIOL; SODIUM COCOYL GLUTAMATE; ALLANTOIN; SODIUM CITRATE, UNSPECIFIED FORM; SODIUM LAURATE; SODIUM SARCOSINATE; CAPRYLYL GLYCOL; BENZOIC ACID; CITRIC ACID MONOHYDRATE; CHLORPHENESIN; PHENOXYETHANOL

Clear Future®Deep Pore Cleanser

Drug Facts

Active ingredient

Salicylic Acid 0.5%.

Purpose

Acne Treatment

Uses

- for the treatment of acne.
- helps clear up acne pimples and allows skin to heal.
- helps prevent new acne pimples from forming.

Warnings

For external use only

When using this product

- skin irritation and dryness is more likely to occur if you use another topical acne medication at the same time. If irritation occurs, only use one topical acne medication at a time.
- avoid contact with eyes. If contact occurs, rinse thoroughly with water.

Stop use and ask a doctor if irritation or redness develops and lasts.

Keep out of reach of children.

If swallowed, get medical help or contact a Poison Control Center right away.

Directions

- clean the skin thoroughly before applying this product.
- cover the entire affected area with a thin layer and rinse thoroughly one to three times daily.
- because excessive drying of the skin may occur, start with one application daily, then gradually increase to two or three times daily if needed or as directed by a doctor.
- if bothersome dryness or peeling occurs, reduce application to once a day or every other day.

Other information

STORAGE: 55°F–85°F

Inactive ingredients

water, glycerin, sodium lauroyl sarcosinate, isopentyldiol, cocamidopropyl betaine, decyl glucoside, cellulose gum, lauryl glucoside, salix alba (willow) bark extract, serenoa serrulata fruit extract, calendula officinalis flower extract, salvia officinalis (sage) leaf extract, hamamelis virginiana (witch hazel) water, polyglyceryl-4 caprate, alpha-glucan oligosaccharide, rhamnose, glucose, glucuronic acid, saccharide isomerate, niacinamide, sodium chloride, disodium cocoyl glutamate, propanediol, sodium cocoyl glutamate, allantoin, sodium citrate, sodium laurate, sodium sarcosinate, caprylyl glycol, benzoic acid, citric acid, chlorphenesin, phenoxyethanol.

Questions or comments?

1.800.272.6663

Monday–Friday

6 a.m.–6 p.m. Pacific time

Distributed by
Arbonne International, LLC
Greenwood, IN 46143 USA

PRINCIPAL DISPLAY PANEL - 118 mL Tube Carton

ARBONNE®

CLEAR
FUTURE®

DEEP PORE
ACNE CLEANSER

SALICYLIC ACID 0.5%

4 fl. oz. / 118 mL